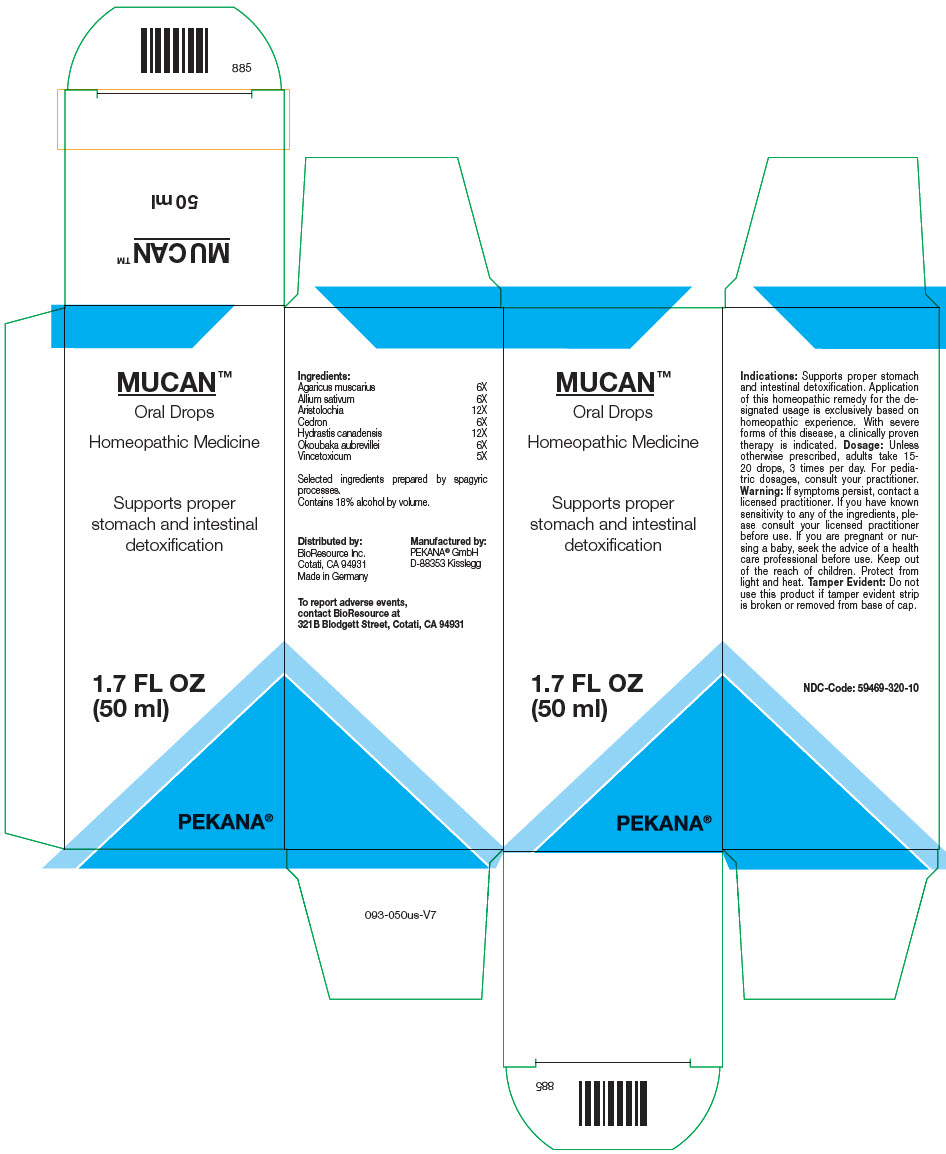 DRUG LABEL: MUCAN
NDC: 59469-320 | Form: SOLUTION/ DROPS
Manufacturer: PEKANA Naturheilmittel GmbH
Category: homeopathic | Type: HUMAN OTC DRUG LABEL
Date: 20230111

ACTIVE INGREDIENTS: AMANITA MUSCARIA FRUITING BODY 6 [hp_X]/50 mL; GARLIC 6 [hp_X]/50 mL; ARISTOLOCHIA CLEMATITIS WHOLE 12 [hp_X]/50 mL; HOMALOLEPIS CEDRON SEED 6 [hp_X]/50 mL; GOLDENSEAL 12 [hp_X]/50 mL; OKOUBAKA AUBREVILLEI BARK 6 [hp_X]/50 mL; VINCETOXICUM HIRUNDINARIA LEAF 5 [hp_X]/50 mL
INACTIVE INGREDIENTS: WATER; ALCOHOL

MUCAN™

ACTIVE INGREDIENT

Ingredients:
Agaricus muscarius | 6X
Allium sativum | 6X
Aristolochia | 12X
Cedron | 6X
Hydrastis canadensis | 12X
Okoubaka aubrevillei | 6X
Vincetoxicum | 5X

Selected ingredients prepared by spagyric processes.

INACTIVE INGREDIENT

Contains 18% alcohol by volume.

Indications

PURPOSE

Supports proper stomach and intestinal detoxification. Application of this homeopathic remedy for the designated usage is exclusively based on homeopathic experience. With severe forms of this disease, a clinically proven therapy is indicated.

Dosage

Unless otherwise prescribed, adults take 15-20 drops, 3 times per day. For pediatric dosages, consult your practitioner.

Warning

ASK DOCTOR

If symptoms persist, contact a licensed practitioner. If you have known sensitivity to any of the ingredients, please consult your licensed practitioner before use. If you are pregnant or nursing a baby, seek the advice of a health care professional before use.

Keep out of the reach of children.

STORAGE AND HANDLING

Protect from light and heat.

Tamper Evident

Do not use this product if tamper evident strip is broken or removed from base of cap.

QUESTIONS

To report adverse events, contact BioResource at 321B Blodgett Street, Cotati, CA 94931

Distributed by:
BioResource Inc.
Cotati, CA 94931

Manufactured by:
PEKANA® GmbH
D-88353 Kisslegg

PRINCIPAL DISPLAY PANEL - 50 ml Bottle Box

MUCAN™
Oral Drops

Homeopathic Medicine

Supports proper
stomach and intestinal
detoxification

1.7 FL OZ
(50 ml)

PEKANA®